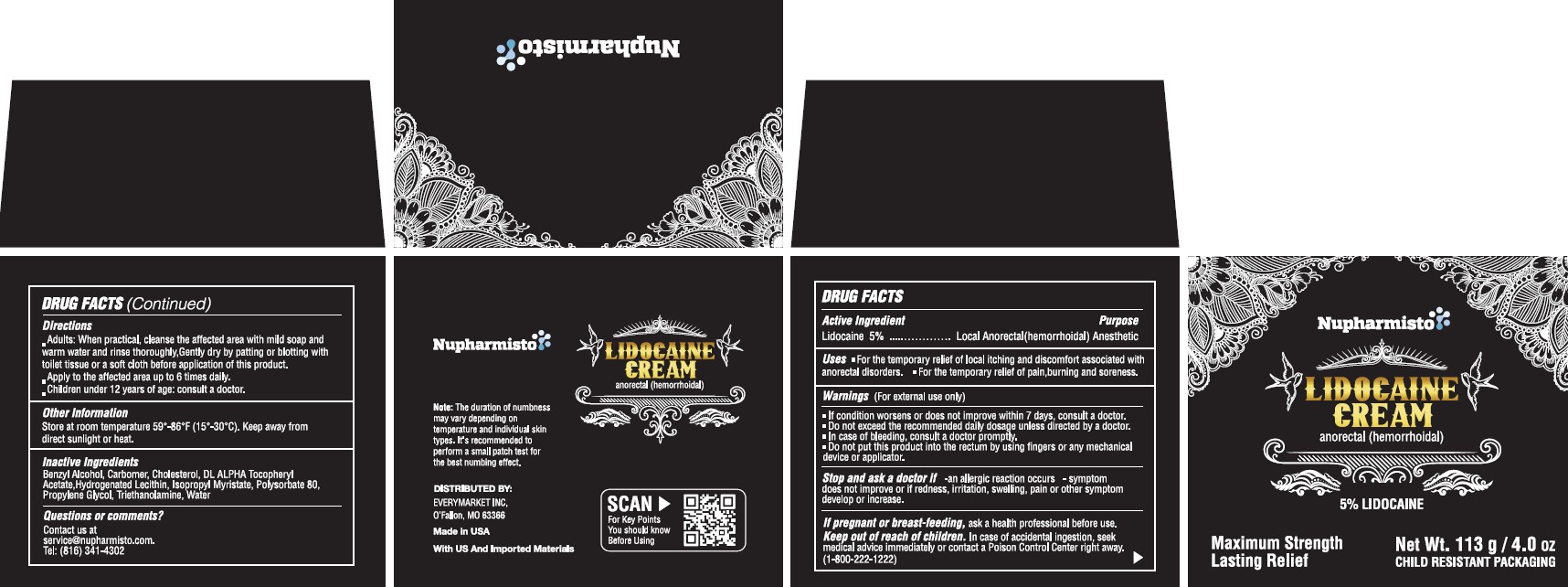 DRUG LABEL: Lidocaine anorectal cream
NDC: 85833-001 | Form: CREAM
Manufacturer: EveryMarket Inc
Category: otc | Type: HUMAN OTC DRUG LABEL
Date: 20251028

ACTIVE INGREDIENTS: LIDOCAINE 5 g/100 g
INACTIVE INGREDIENTS: WATER; ISOPROPYL MYRISTATE; POLYSORBATE 80; PROPYLENE GLYCOL; BENZYL ALCOHOL; CARBOMER; TRIETHANOLAMINE; .ALPHA.-TOCOPHEROL ACETATE, DL-; LECITHIN, SUNFLOWER; CHOLESTEROL

5% Lidocaine Cream

Active Ingredient Purpose

Lidocaine 5% Local Anorectal(hemorrhoidal) Anesthetic

INDICATIONS AND USAGE

Uses •For the temporary relief of local itching and discomfort associated with anorectal disorders. • For temporary relief of pain,burning and soreness.

Directions

Adults: When practical, cleanse the affected area with mild soap and warm water and rinse thoroughly.Gently dry by patting or blotting with toilet tissue or a soft cloth before application of this product.
• Apply to the affected area up to 6 times daily.
Children under 12 years of age: consult a doctor

Warnings (For external use only)

• If condition worsens or does not improve within 7 days, consult a doctor.

• Do not exceed the recommended daily dosage unless directed by a doctor.
• In case of bleeding, consult a doctor promptly.
• Do not put this product into the rectum by using fingers or any mechanical device or applicator.
Stop and ask a doctor if -an allergic reaction occurs - symptom does not improve or if redness, irritation, swelling, pain or other symptom develop or increase.

Keep out of reach of children

. In case of accidental ingestion, seek medical advice immediately or contact a Poison Control Center right away.
(1-800-222-1222)

Inactive ingredients

Benzyl Alcohol, Carbomer, Cholesterol, DL ALPHA Tocopheryl Acetate.Hydrogenated Lecithin, lsopropyl Myristate, Polysorbate80, Propylene Glycol, Triethanolamine, Water